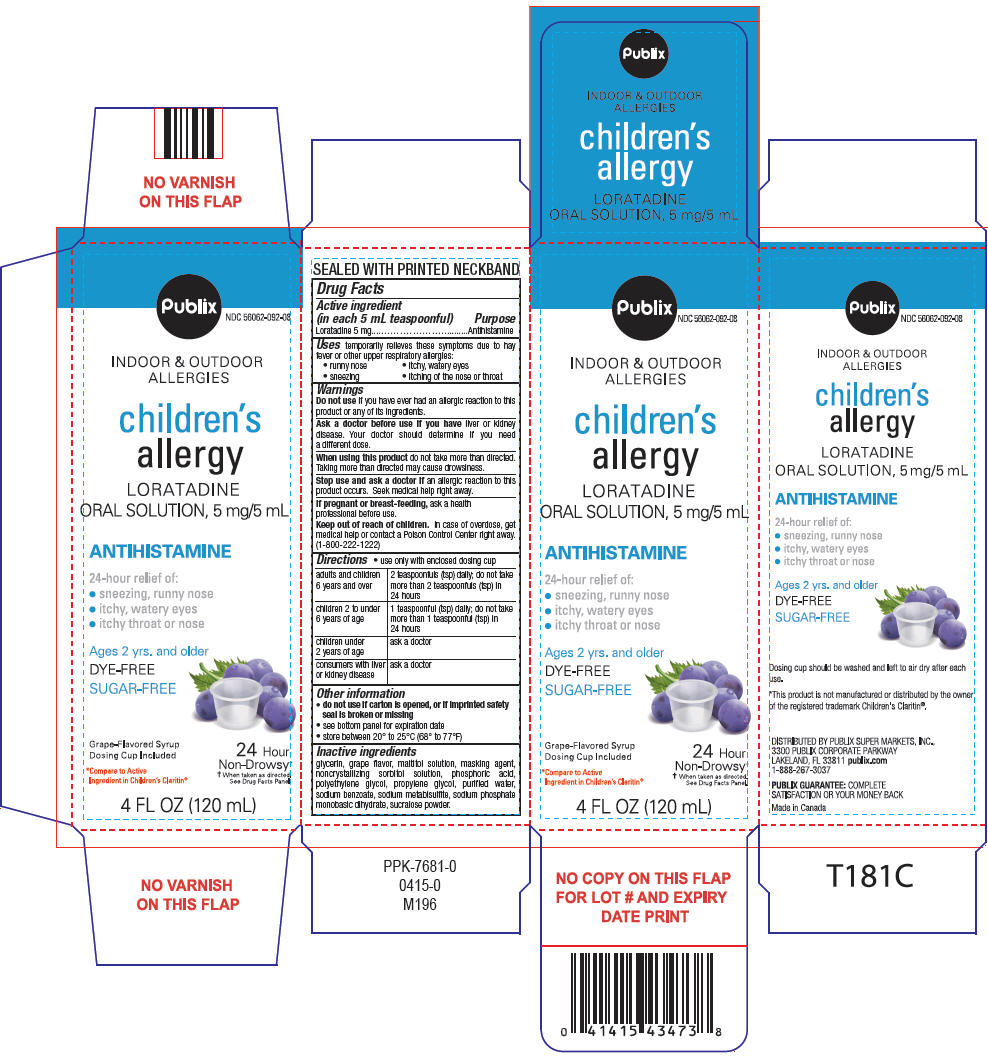 DRUG LABEL: childrens allergy
NDC: 56062-092 | Form: SOLUTION
Manufacturer: Publix Super Markets Inc
Category: otc | Type: HUMAN OTC DRUG LABEL
Date: 20250715

ACTIVE INGREDIENTS: LORATADINE 5 mg/5 mL
INACTIVE INGREDIENTS: GLYCERIN; SORBITOL; PHOSPHORIC ACID; POLYETHYLENE GLYCOL, UNSPECIFIED; PROPYLENE GLYCOL; WATER; SODIUM BENZOATE; SODIUM METABISULFITE; SODIUM PHOSPHATE, MONOBASIC, DIHYDRATE

children's allergy

Drug Facts

Active ingredient (in each 5 mL teaspoonful)

Loratadine 5 mg

Purpose

Antihistamine

Uses

temporarily relieves these symptoms due to hay fever or other upper respiratory allergies:

- runny nose
- itchy, watery eyes
- sneezing
- itching of the nose or throat

Warnings

DO NOT USE

Do not useif you have ever had an allergic reaction to this product or any of its ingredients.

Ask a doctor before use if you haveliver or kidney disease. Your doctor should determine if you need a different dose.

WHEN USING

When using this productdo not take more than directed. Taking more than directed may cause drowsiness.

Stop use and ask a doctor ifan allergic reaction to this product occurs. Seek medical help right away.

PREGNANCY OR BREAST FEEDING

If pregnant or breast-feeding,ask a health professional before use.

Keep out of reach of children.In case of overdose, get medical help or contact a Poison Control Center right away. (1-800-222-1222)

Directions

- use only with enclosed dosing cup

adults and children 6 years and over | 2 teaspoonfuls (tsp) daily; do not take more than 2 teaspoonfuls (tsp) in 24 hours
children 2 to under 6 years of age | 1 teaspoonful (tsp) daily; do not take more than 1 teaspoonful (tsp) in 24 hours
children under 2 years of age | ask a doctor
consumers with liver or kidney disease | ask a doctor

Other information

- do not use if carton is opened, or if imprinted safety seal is broken or missing
- see bottom panel for expiration date
- store between 20° to 25°C (68° to 77°F)

Inactive ingredients

glycerin, grape flavor, maltitol solution, masking agent, noncrystallizing sorbitol solution, phosphoric acid, polyethylene glycol, propylene glycol, purified water, sodium benzoate, sodium metabisulfite, sodium phosphate monobasic dihydrate, sucralose powder.

DISTRIBUTED BY PUBLIX SUPER MARKETS, INC.,
3300 PUBLIX CORPORATE PARKWAY
LAKELAND, FL 33811

PRINCIPAL DISPLAY PANEL - 120 mL Bottle Carton

Publix

NDC 56062-092-08

INDOOR & OUTDOOR ALLERGIES

children's allergy

LORATADINE
ORAL SOLUTION, 5 mg/5 mL

ANTIHISTAMINE

24-hour relief of:

- sneezing, runny nose
- itchy, watery eyes
- itchy throat or nose

Ages 2 yrs. and older

DYE FREE

SUGAR-FREE

Grape-Flavored Syrup

Dosing Cup Enclosed

*Compare to Active
Ingredient in Children's Claritin®

24 Hour
Non-Drowsy†
†When taken as directed.
See Drug Facts Panel

4 FL OZ (120 mL)